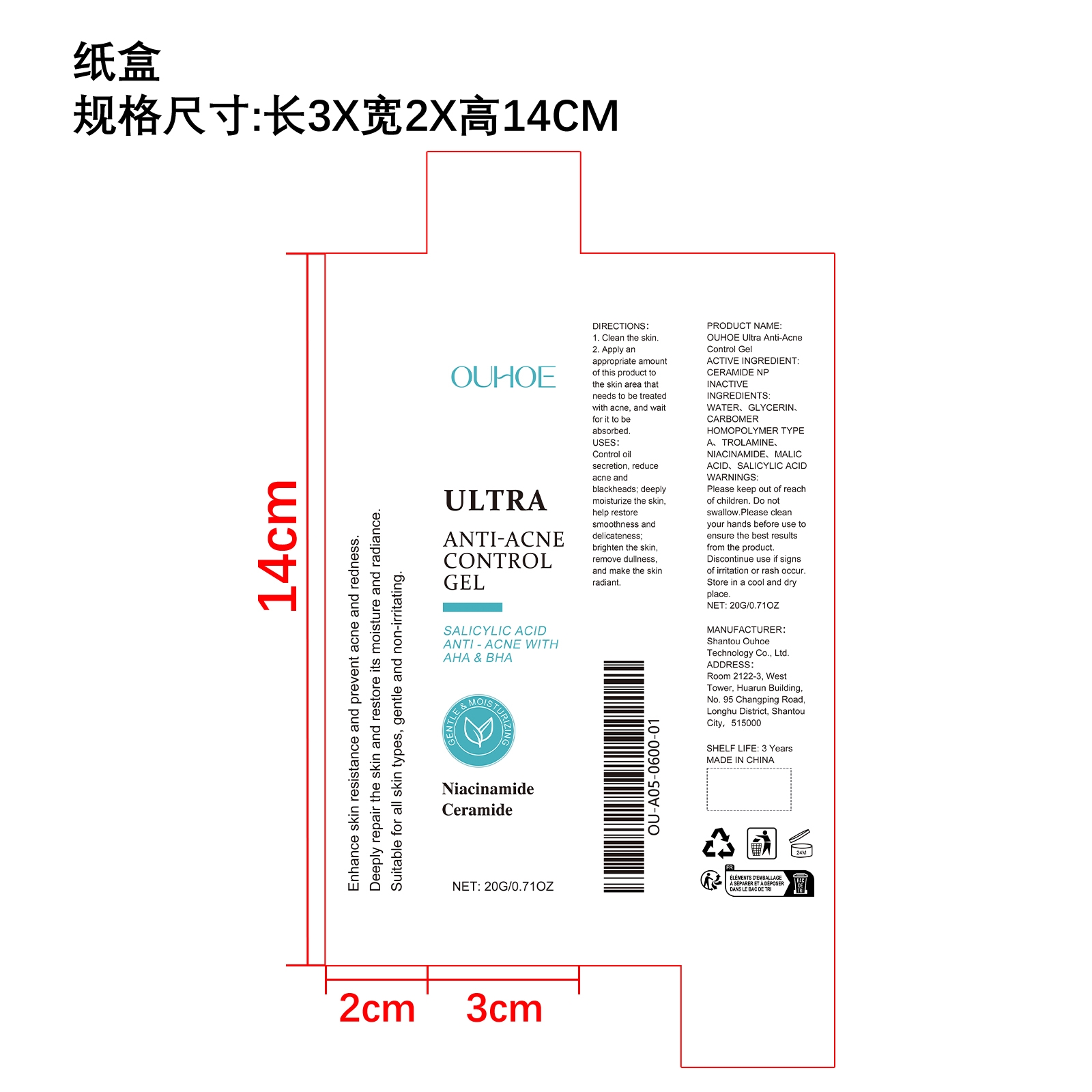 DRUG LABEL: OUHOE Ultra Anti-Acne Control Gel
NDC: 85163-006 | Form: GEL
Manufacturer: Shantou Ouhoe Technology Co., Ltd.
Category: otc | Type: HUMAN OTC DRUG LABEL
Date: 20251127

ACTIVE INGREDIENTS: CERAMIDE NP 0.004 mg/20 mg
INACTIVE INGREDIENTS: CARBOMER HOMOPOLYMER TYPE A 0.04 mg/20 mg; GLYCERIN 1.6 mg/20 mg; WATER 18.304 mg/20 mg; TROLAMINE 0.04 mg/20 mg; NIACINAMIDE 0.004 mg/20 mg; SALICYLIC ACID 0.004 mg/20 mg; MALIC ACID 0.004 mg/20 mg

ACTIVE INGREDIENT

CERAMIDE NP

WHEN USING

1. Clean the skin.

2. Apply an appropriate amount of this product to the skin area that needs to be treated with acne, and wait for it to be absorbed.

PURPOSE

Control oil secretion, reduce acne and blackheads; deeply moisturize the skin, help restore smoothness and delicateness; brighten the skin, remove dullness, and make the skin radiant.

WARNINGS

Please keep out of reach of children. Do not swallow.Please clean your hands before use to ensure the best results from the product. Discontinue use if signs of irritation or rash occur. Store in a cool and dry place.

DO NOT USE

Discontinue use if signs of irritation or rash occur.

STOP USE

Discontinue use if signs of irritation or rash occur.

KEEP OUT OF REACH OF CHILDREN

Please keep out of reach of children. Do not swallow.

STORAGE AND HANDLING

Store in a cool and dry place.

INACTIVE INGREDIENT

WATER、GLYCERIN、CARBOMER HOMOPOLYMER TYPE A、TROLAMINE、NIACINAMIDE、MALIC ACID、SALICYLIC ACID

DOSAGE AND ADMINISTRATION

1. Clean the skin.

2. Apply an appropriate amount of this product to the skin area that needs to be treated with acne, and wait for it to be absorbed.

INDICATIONS AND USAGE

Control oil secretion, reduce acne and blackheads; deeply moisturize the skin, help restore smoothness and delicateness; brighten the skin, remove dullness, and make the skin radiant.